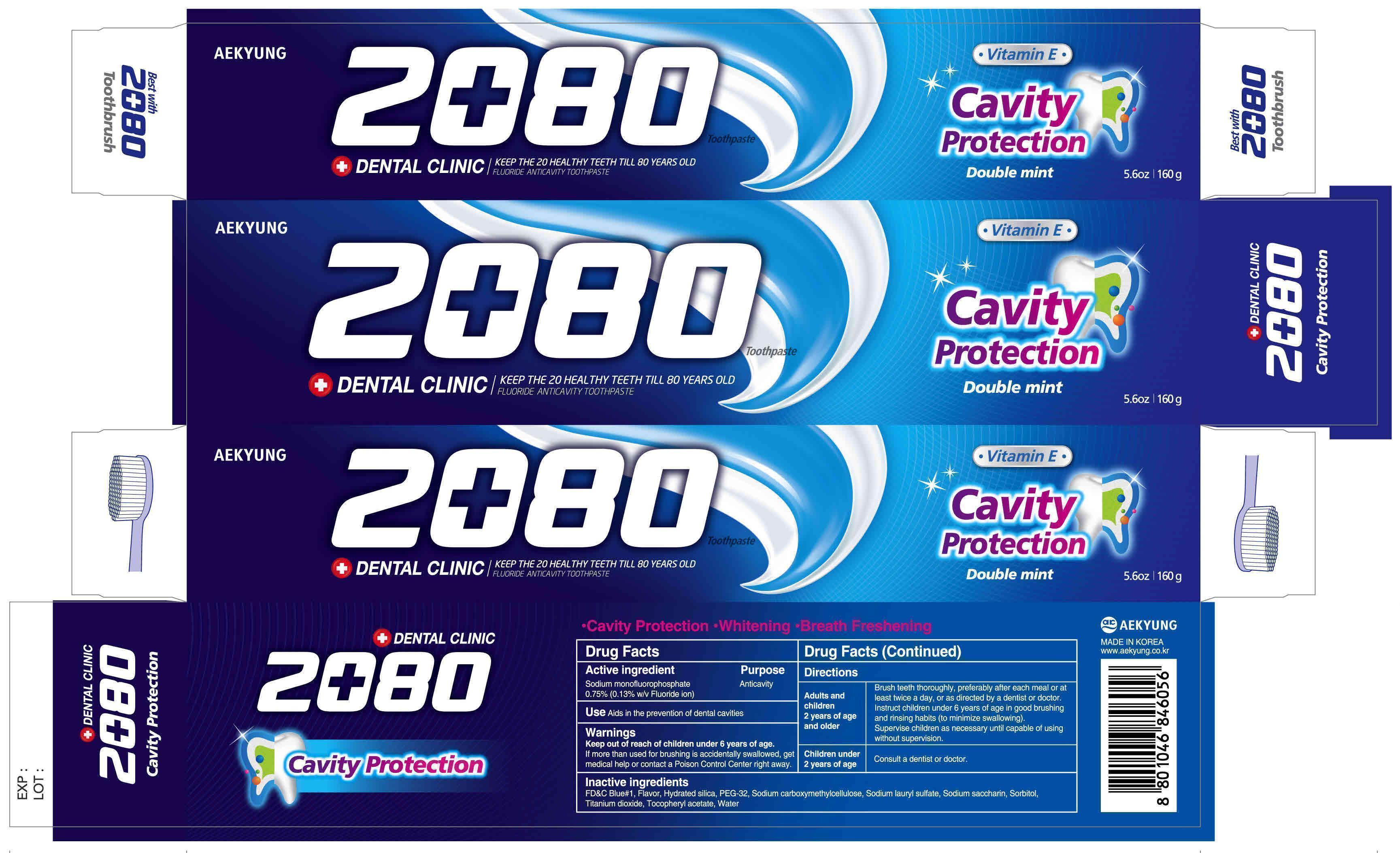 DRUG LABEL: Dental Clinic 2080 Cavity Protection
NDC: 67225-0001 | Form: PASTE
Manufacturer: Aekyung Industrial Co., Ltd.
Category: otc | Type: HUMAN OTC DRUG LABEL
Date: 20160714

ACTIVE INGREDIENTS: SODIUM MONOFLUOROPHOSPHATE 0.208 g/160 g
INACTIVE INGREDIENTS: SORBITOL 92.8 g/160 g; SODIUM LAURYL SULFATE 3.52 g/160 g; CARBOXYMETHYLCELLULOSE SODIUM 0.64 g/160 g; TITANIUM DIOXIDE 0.4 g/160 g; SACCHARIN SODIUM 0.208 g/160 g; ALPHA-TOCOPHEROL ACETATE 0.4 g/160 g

WARNINGS

If more than used for brushing is accidentally swallowed, get medical help or contact a Poison Control Center right away

Keep out of reach of children under 6 years of age

ACTIVE INGREDIENT

Sodium monofluorophosphate 0.75% (0.13% w/v Fluoride ion)

INACTIVE INGREDIENT

Sodium carboxymethylcellulose, Sodium lauryl sulfate, Sodium saccharin, Sorbitol, Titanium dioxide, Tocopheryl acetate, water

Purpose Anticavity

DOSAGE AND ADMINISTRATION

Adults and children 2 years of age and older

Brush teeth thoroughly, preferably after each meal or at least twice a day or as directed by a dentist or doctor.

Instruct children under 6 years of age in good brushing ad rinsing habits (to minimize swallowing).

Supervise children as necessary until capable of using without supervision.

Children under 2 years of age

Consult a dentist or doctor

INDICATIONS AND USAGE

Aids in the prevention of dental cavities